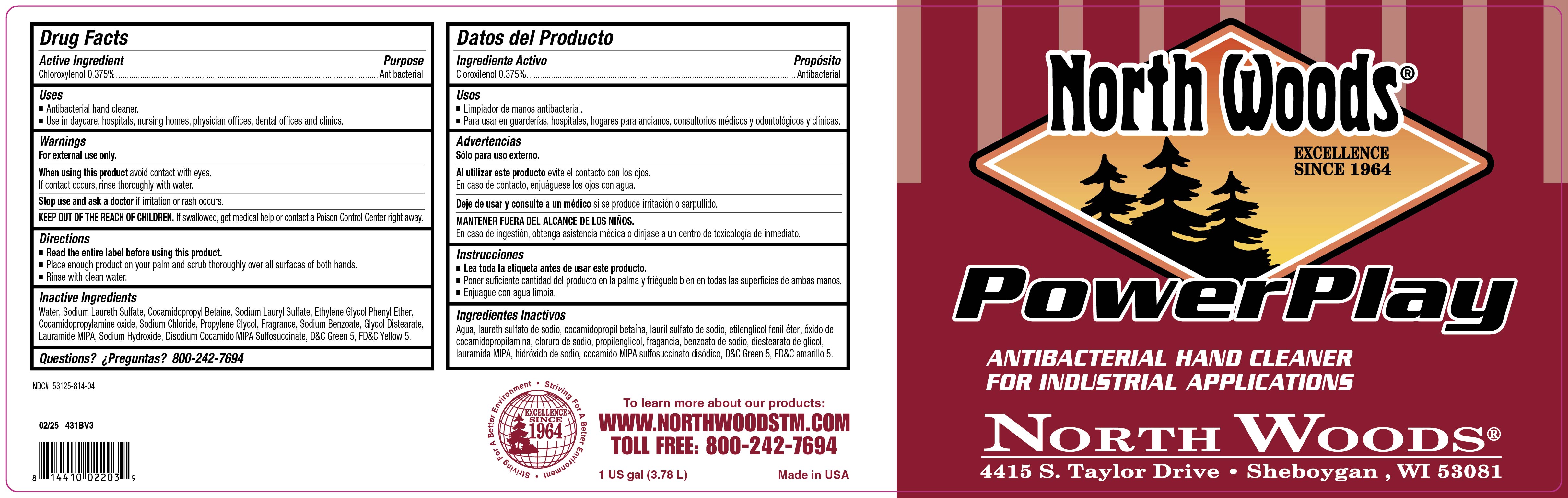 DRUG LABEL: NorthWoods PowerPlay
NDC: 53125-814 | Form: LIQUID
Manufacturer: Northwoods PowerPlay
Category: otc | Type: HUMAN OTC DRUG LABEL
Date: 20251008

ACTIVE INGREDIENTS: CHLOROXYLENOL 0.375 g/100 mL
INACTIVE INGREDIENTS: VERDYL ACETATE; ETHYLENE OXIDE; SODIUM ALUMINIUM SILICATE; D&C GREEN NO. 5; FD&C YELLOW NO. 5; SODIUM BENZOATE; PHENOXYETHANOL; COCAMIDOPROPYL BETAINE; .ALPHA.-HEXYLCINNAMALDEHYDE; .ALPHA.-AMYLCINNAMALDEHYDE; BENZYL SALICYLATE; .GAMMA.-UNDECALACTONE; WATER; SODIUM CHLORIDE; 2-TERT-BUTYLCYCLOHEXYL ACETATE; CALCIUM SILICATE; LINALOOL; TRIBASIC CALCIUM PHOSPHATE; COCAMIDOPROPYLAMINE OXIDE; 1-(2,3,8,8-TETRAMETHYL-1,2,3,4,5,6,7,8-OCTAHYDRONAPHTHALEN-2-YL)ETHANONE; .BETA.-CITRONELLOL, (+/-)-; 3-(3,4-METHYLENEDIOXYPHENYL)-2-METHYLPROPANAL; HEXYL SALICYLATE; PROPYLENE GLYCOL; ETHYLENE BRASSYLATE; 2,6-DIMETHYL-5-HEPTENAL; LAURIC ISOPROPANOLAMIDE; SODIUM LAURYL SULFATE; SODIUM LAURETH SULFATE; 4-ACETOXY-3-PENTYLTETRAHYDROPYRAN; DIHYDROMYRCENOL; PHENYLETHYL ALCOHOL; BENZYL ACETATE; SODIUM HYDROXIDE; GLYCOL DISTEARATE; HEXAHYDRO-4,7-METHANOINDEN-6-YL PROPIONATE; SODIUM CARBONATE; 2-ISOBUTYL-4-METHYLTETRAHYDROPYRAN-4-OL

Northwoods PowerPlay

doasge

Place enough product on palms and scurb thoroughly over all surfaces of both hands

inactive ingredients

Water, Sodium Laureth Sulfate, Cocamidopropyl Betaine, Sodium Lauryl Sufate, Ethylen Glycol Phenyl Ether, Cocamidopropyle Amine Oxide,Sodium Chloride, Propylene Glycol, Fragrance, Sodium Benzoate, Glycol Distearate, Lauramide MIPA, Sdoium Hydroxide, Disodium Cocamido,MIPA Sulfosuccinate, D&C Green 5, FD&C Yellow 5

instructions for use

Place enough product on your palm and scrub thoroughly over all surfaces of both hands. Rinse with Clean water

active

Chloroxylenol

KEEP OUT OF REACH OF CHILDREN. If swallowed get medical help or contact Poison Control center right away

purpose

Antibacterial

warning

For external use only

When using this product aboid contact with eyes

If Contact occurs rinse thoroughly wiht water

Stop use and ask a doctor if rritation or rash occurs

usage

Antibacterial Hand Cleaner

Use in Daycare, Hospitals, Nursing Homes, physicians offices, dental offices and clinics